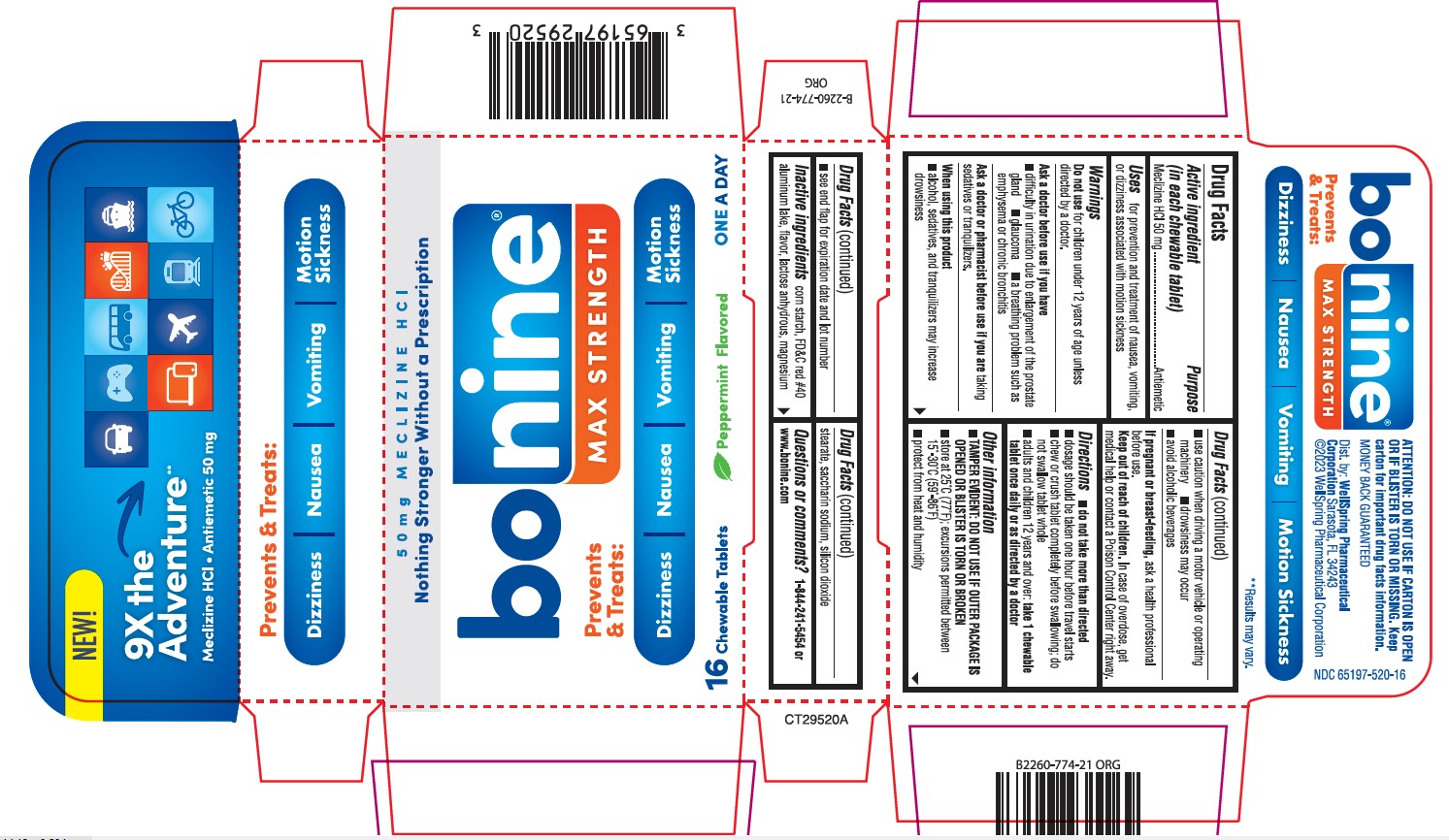 DRUG LABEL: BONINE MAX
NDC: 65197-520 | Form: TABLET, CHEWABLE
Manufacturer: WellSpring Pharmaceutical Corporation
Category: otc | Type: HUMAN OTC DRUG LABEL
Date: 20250411

ACTIVE INGREDIENTS: MECLIZINE HYDROCHLORIDE 50 mg/1 1
INACTIVE INGREDIENTS: ANHYDROUS LACTOSE; STARCH, CORN; PEPPERMINT; FD&C RED NO. 40; SACCHARIN SODIUM; MAGNESIUM STEARATE; SILICON DIOXIDE

BONINE®
MECLIZINE HYDROCHLORIDE • ANTIEMETIC

Active ingredient (in each tablet)

Meclizine HCl 50 mg

Purpose

Antiemetic

Uses

prevents and treats nausea, vomiting or dizziness associated with motion sickness

Warnings

Do not use

for children under 12 years of age unless directed by a doctor.

Ask a doctor before use if you have

- difficulty in urination due to enlargement of the prostate gland
- glaucoma
- a breathing problem such as emphysema or chronic bronchitis

Ask a doctor or pharmacist before use if you are

taking sedatives or tranquilizers.

When using this product

- alcohol, sedatives, and tranquilizers may increase drowsiness
- use caution when driving a motor vehicle or operating machinery
- drowsiness may occur
- avoid alcoholic drinks

If pregnant or breast-feeding

ask a health professional before use.

Keep out of reach of children

In case of overdose, get medical help or contact a Poison Control Center right away

Directions

• do not take more than directed

• dosage should be taken one hour before travel starts

• Chew or crush tablet completely before swallowing; do not swallow tablet whole

• adults and children 12 years of age and over: take 1 chewable tablet once daily or as directed by a doctor.

Other information

- store at 25°C (77°F); excursions permitted between 15° - 30°C (59° - 86°F)
- protect from heat and humidity
- see end flap for expiration date and lot number

Inactive ingredients

corn starch, FD&C red #40 aluminum lake, flavor, lactose anhydrous, magnesium stearate, sodium saccharin, silicon dioxide

Questions?

call toll-free 1 (844) 241-5454 or visit us on the web at www.bonine.com

NDC 65197-520-16

BONINE MAX STRENGTH

Prevents and treats: Dizziness - Nausea - Vomiting - Motion sickness

** Results may vary

ATTENTION: DO NOT USE IF CARTON IS OPEN OR IF BLISTER IS TORN OR MISSING. Keep carton for important drug facts information.

MONEY BACK GUARANTEED

Dist. by: WellSpring Pharmaceutical Corporation
Sarasota, FL 34243 USA

© 2023 WellSpring Pharmaceutical Corporation

PRINCIPAL DISPLAY PANEL

NEW!

9x the Adventure**

Meclizine HCL - Antiemetic 50 mg

Prevents and treats: Dizziness - Nausea - Vomiting - Motion sickness

50 mg MECLIZINE HCL

Nothing Stronger without a Prescription
Bonine MAX